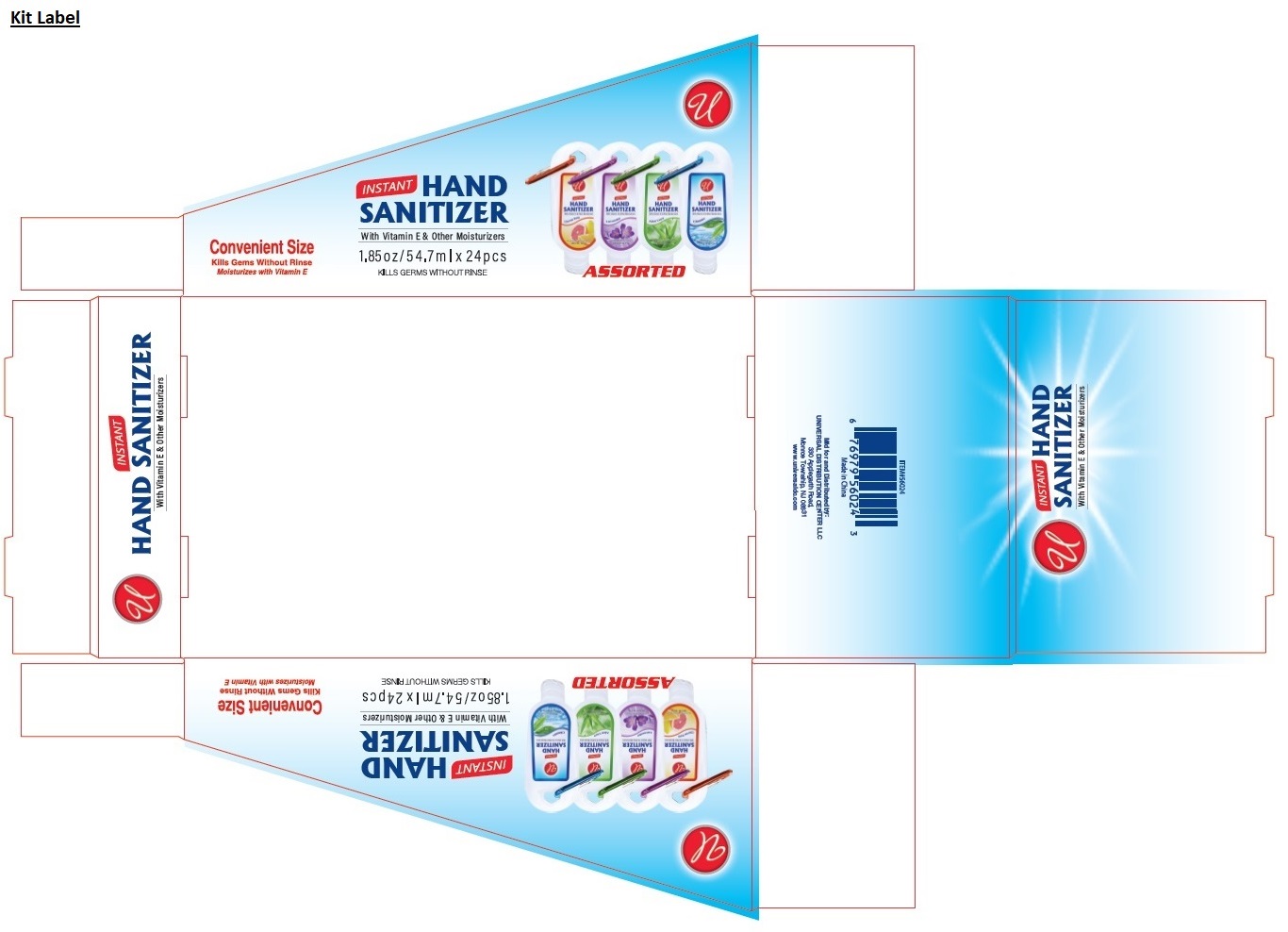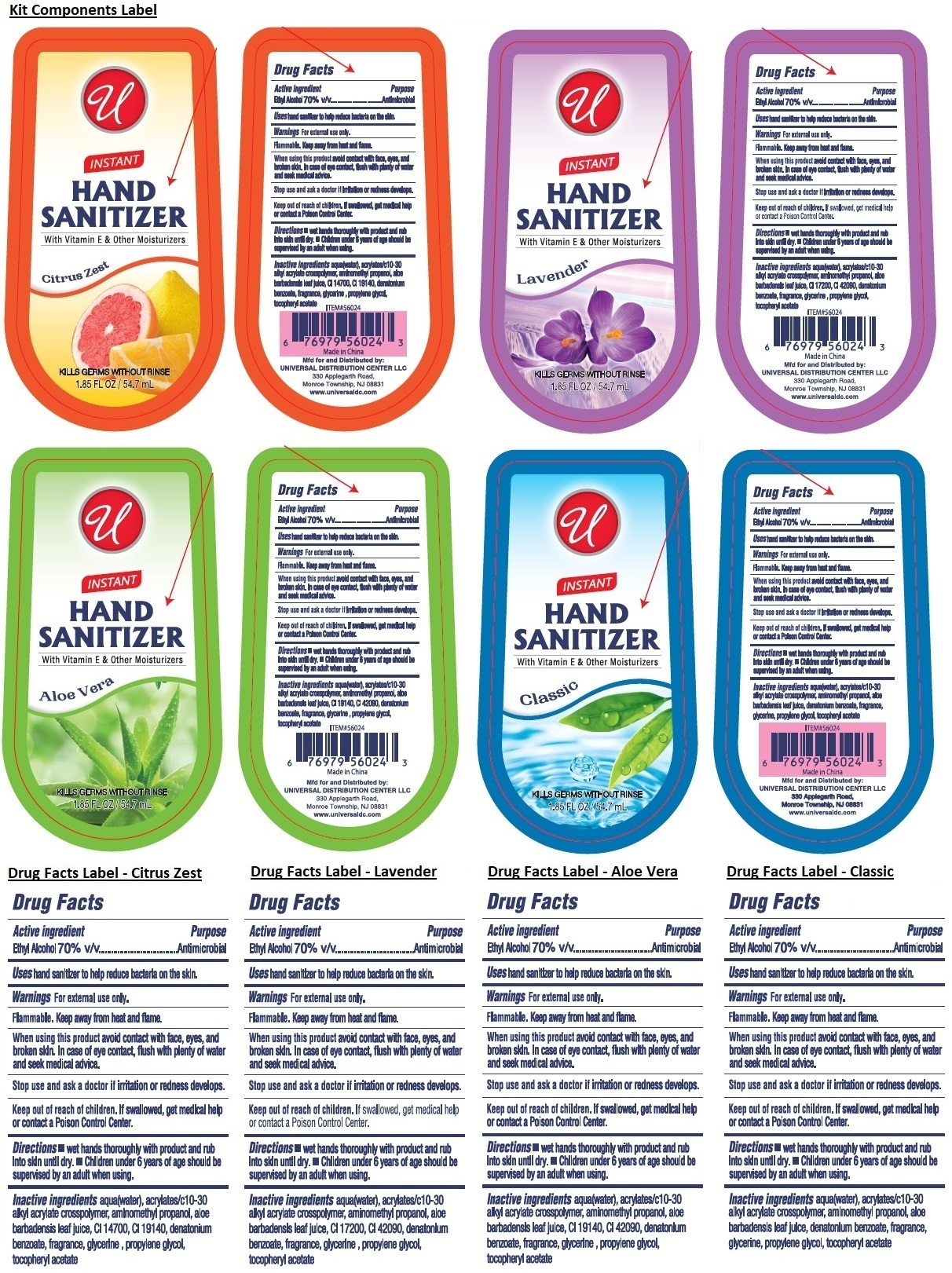 DRUG LABEL: W/CLIP PDQ INSTANT HAND SANITIZER
NDC: 52000-423 | Form: KIT | Route: TOPICAL
Manufacturer: Universal Distribution Center LLC
Category: otc | Type: HUMAN OTC DRUG LABEL
Date: 20250408

ACTIVE INGREDIENTS: ALCOHOL 70 mL/100 mL; ALCOHOL 70 mL/100 mL; ALCOHOL 70 mL/100 mL; ALCOHOL 70 mL/100 mL
INACTIVE INGREDIENTS: WATER; ACRYLATES/C10-30 ALKYL ACRYLATE CROSSPOLYMER (60000 MPA.S); AMINOMETHYLPROPANOL; ALOE VERA LEAF JUICE; FD&C RED NO. 4; FD&C YELLOW NO. 5; DENATONIUM BENZOATE; GLYCERIN; PROPYLENE GLYCOL; .ALPHA.-TOCOPHEROL ACETATE; WATER; ACRYLATES/C10-30 ALKYL ACRYLATE CROSSPOLYMER (60000 MPA.S); AMINOMETHYLPROPANOL; ALOE VERA LEAF JUICE; D&C RED NO. 33; FD&C BLUE NO. 1; DENATONIUM BENZOATE; GLYCERIN; PROPYLENE GLYCOL; .ALPHA.-TOCOPHEROL ACETATE; WATER; ACRYLATES/C10-30 ALKYL ACRYLATE CROSSPOLYMER (60000 MPA.S); AMINOMETHYLPROPANOL; ALOE VERA LEAF JUICE; FD&C YELLOW NO. 5; FD&C BLUE NO. 1; DENATONIUM BENZOATE; GLYCERIN; PROPYLENE GLYCOL; .ALPHA.-TOCOPHEROL ACETATE; WATER; ACRYLATES/C10-30 ALKYL ACRYLATE CROSSPOLYMER (60000 MPA.S); AMINOMETHYLPROPANOL; ALOE VERA LEAF JUICE; DENATONIUM BENZOATE; GLYCERIN; PROPYLENE GLYCOL; .ALPHA.-TOCOPHEROL ACETATE

W/CLIP PDQ INSTANT HAND SANITIZER

INSTANT HAND SANITIZER Citrus Zest

Drug Facts

Active ingredient

Ethyl Alcohol 70% v/v

Purpose

Antimicrobial

Uses

hand sanitizer to help reduce bacteria on the skin.

Warnings

For external use only.

Flammable. Keep away from heat and flame.

When using this product avoid contact with face, eyes, and broken skin. In case of eye contact, flush with plenty of water and seek medical advice.

Stop use and ask a doctor if irritation or redness develops.

Keep out of reach of children. If swallowed, get medical help or contact a Poison Control Center.

Directions

• wet hands thoroughly with product and rub into skin until dry. • Children under 6 years of age should be supervised by an adult when using.

Inactive ingredients

aqua(water), acrylates/c10-30 alkyl acrylate crosspolymer, aminomethyl propanol, aloe barbadensis leaf juice, CI 14700, CI 19140, denatonium benzoate, fragrance, glycerine, propylene glycol, tocopheryl acetate

INSTANT HAND SANITIZER Lavender

Drug Facts

Active ingredient

Ethyl Alcohol 70% v/v

Purpose

Antimicrobial

Uses

hand sanitizer to help reduce bacteria on the skin.

Warnings

For external use only.

Flammable. Keep away from heat and flame.

When using this product avoid contact with face, eyes, and broken skin. In case of eye contact, flush with plenty of water and seek medical advice.

Stop use and ask a doctor if irritation or redness develops.

Keep out of reach of children. If swallowed, get medical help or contact a Poison Control Center.

Directions

• wet hands thoroughly with product and rub into skin until dry. • Children under 6 years of age should be supervised by an adult when using.

Inactive ingredients

aqua(water), acrylates/c10-30 alkyl acrylate crosspolymer, aminomethyl propanol, aloe barbadensis leaf juice, CI 17200, CI 42090, denatonium benzoate, fragrance, glycerine, propylene glycol, tocopheryl acetate

INSTANT HAND SANITIZER Aloe Vera

Drug Facts

Active ingredient

Ethyl Alcohol 70% v/v

Purpose

Antimicrobial

Uses

hand sanitizer to help reduce bacteria on the skin.

Warnings

For external use only.

Flammable. Keep away from heat and flame.

When using this product avoid contact with face, eyes, and broken skin. In case of eye contact, flush with plenty of water and seek medical advice.

Stop use and ask a doctor if irritation or redness develops.

Keep out of reach of children. If swallowed, get medical help or contact a Poison Control Center.

Directions

• wet hands thoroughly with product and rub into skin until dry. • Children under 6 years of age should be supervised by an adult when using.

Inactive ingredients

aqua(water), acrylates/c10-30 alkyl acrylate crosspolymer, aminomethyl propanol, aloe barbadensis leaf juice, CI 19140, CI 42090, denatonium benzoate, fragrance, glycerine, propylene glycol, tocopheryl acetate

INSTANT HAND SANITIZER Classic

Drug Facts

Active ingredient

Ethyl Alcohol 70% v/v

Purpose

Antimicrobial

Uses

hand sanitizer to help reduce bacteria on the skin.

Warnings

For external use only.

Flammable. Keep away from heat and flame.

When using this product avoid contact with face, eyes, and broken skin. In case of eye contact, flush with plenty of water and seek medical advice.

Stop use and ask a doctor if irritation or redness develops.

Keep out of reach of children. If swallowed, get medical help or contact a Poison Control Center.

Directions

• wet hands thoroughly with product and rub into skin until dry. • Children under 6 years of age should be supervised by an adult when using.

Inactive ingredients

aqua(water), acrylates/c10-30 alkyl acrylate crosspolymer, aminomethyl propanol, aloe barbadensis leaf juice, denatonium benzoate, fragrance, glycerine, propylene glycol, tocopheryl acetate

With Vitamin E & Other Moisturizers

KILLS GERMS WITHOUT RINSE

Convenient Size

Moisturizes with Vitamin E

ASSORTED

Made in China

Mfd for and Distributed by:
UNIVERSAL DISTRIBUTION CENTER LLC
330 Applegarth Road,
Monroe Township, NJ 08831
www.universaldc.com